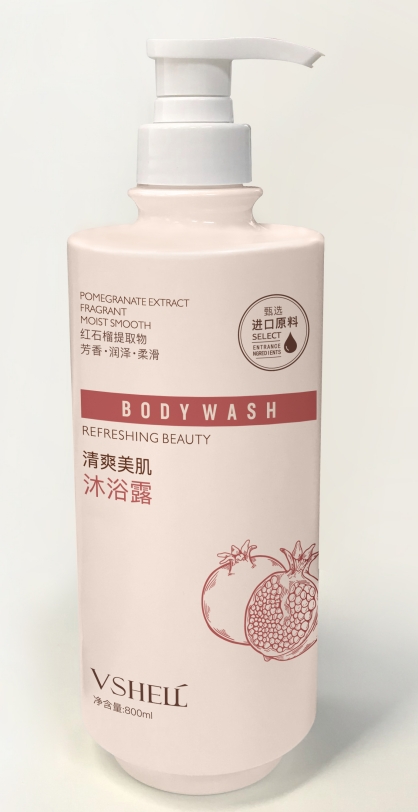 DRUG LABEL: Whitening Shower Gel
NDC: 84507-017 | Form: GEL
Manufacturer: Guangdong Miaolian Cosmetics Co., Ltd.
Category: otc | Type: HUMAN OTC DRUG LABEL
Date: 20240820

ACTIVE INGREDIENTS: 3-O-ETHYL ASCORBIC ACID 0.4 mg/100 mL
INACTIVE INGREDIENTS: WATER

DOSAGE AND ADMINISTRATION

Apply to a body sponge on damp skin, rub into a rich lather all over the body, then rinse thoroughly.

WARNINGS

For External Use only.
When using this product avoid contact with eyes. If contact occurs, rinse eyes thoroughly with water.
Stop use and ask a doctor
irritation or redness develops - condition persists for more than 72 hours.
Keep out of reach of children.
If swallowed, get medical help or contact a Poison Control Center right away

INACTIVE INGREDIENT

water...

INDICATIONS AND USAGE

For washing to decrease bacteria on the skin

Keep out of reach of children.

PURPOSE

Help to whiten
If used with other whitening products, it can remove dark spots and the risk of early skin aging